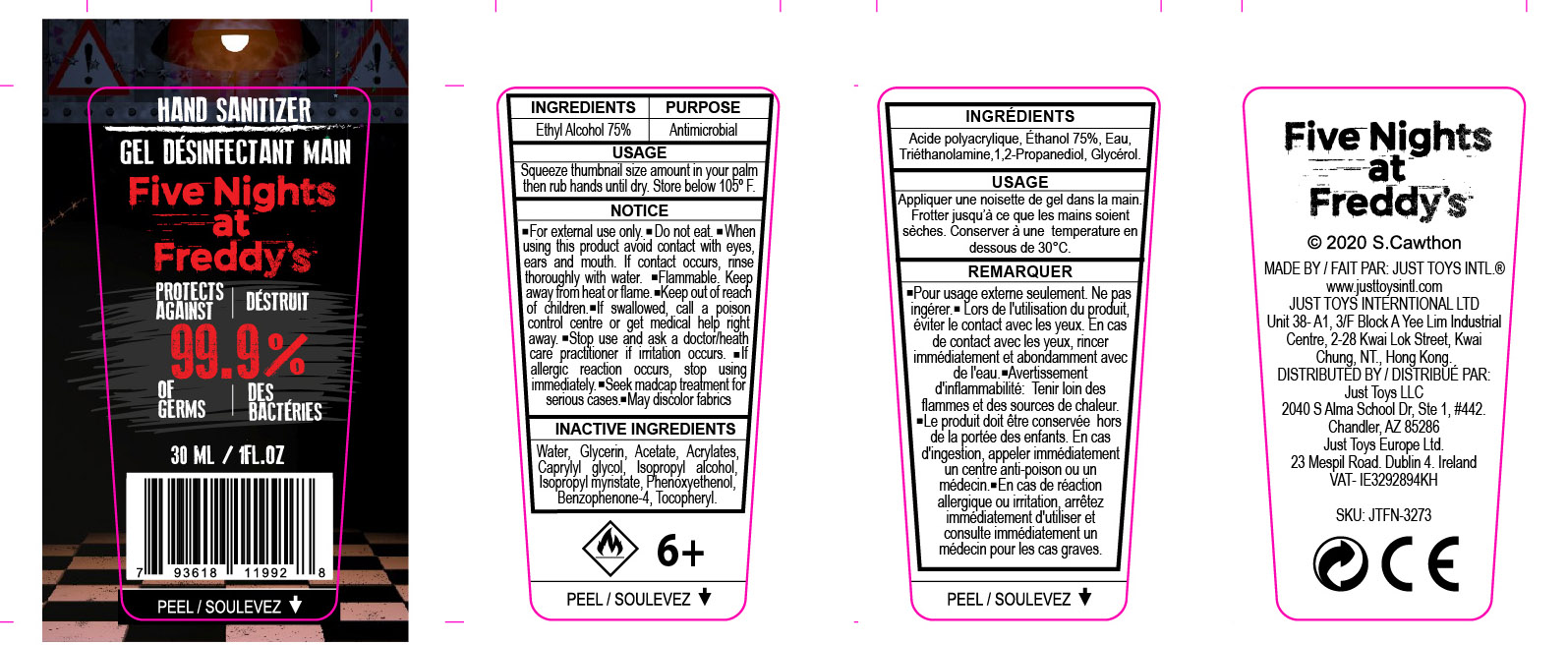 DRUG LABEL: Hand Sanitizer
NDC: 77742-002 | Form: GEL
Manufacturer: Just Toys LLC
Category: otc | Type: HUMAN OTC DRUG LABEL
Date: 20201021

ACTIVE INGREDIENTS: ALCOHOL 75 mL/100 mL
INACTIVE INGREDIENTS: GLYCERIN 1.45 mL/100 mL; ISOPROPYL ALCOHOL 0.125 mL/100 mL; WATER

Active Ingredient(s)

Ethyl Alcohol 75% v/v. Purpose: Antimicrobial

Purpose

Antimicrobial, Hand Sanitizer

Use

Hand Sanitizer to help reduce bacteria that potentially can cause disease. For use when soap and water are not available.

Warnings

For external use only. Do not eat. When using this product avoid contact with eyes, ears and mouth. Flammable. Keep away from heat or flame. Keep out of reach of children. If swallowed, call a poison control center or get medical help right away. Stop use and ask a doctor/health care practitioner if irritation occurs. If allergic reaction occurs, stop using immediately. Seek medcap treatment for serious cases. May discolor fabrics.

Do not use

For ages 6 and up.

Directions

Squeeze thumbnail size amount in your palm then rub hands until dry.

Inactive ingredients

water, glycerin, acetate, acrylates, caprylyl glycol, isopropyl alcohol, isopropyl myristate, phenoxyethenol, benzophenone-4, tocopheryl.

RECENT MAJOR CHANGES

Updated our label to match your requirements and remove/edit some of ours. New label attached.

Keep out of reach of children.

Package Label - Principal Display Panel

30 ml NDC: 77742-002-01

PACKAGE LABEL

FNADF_HANGTAG_HAND SANITIZER.jpg